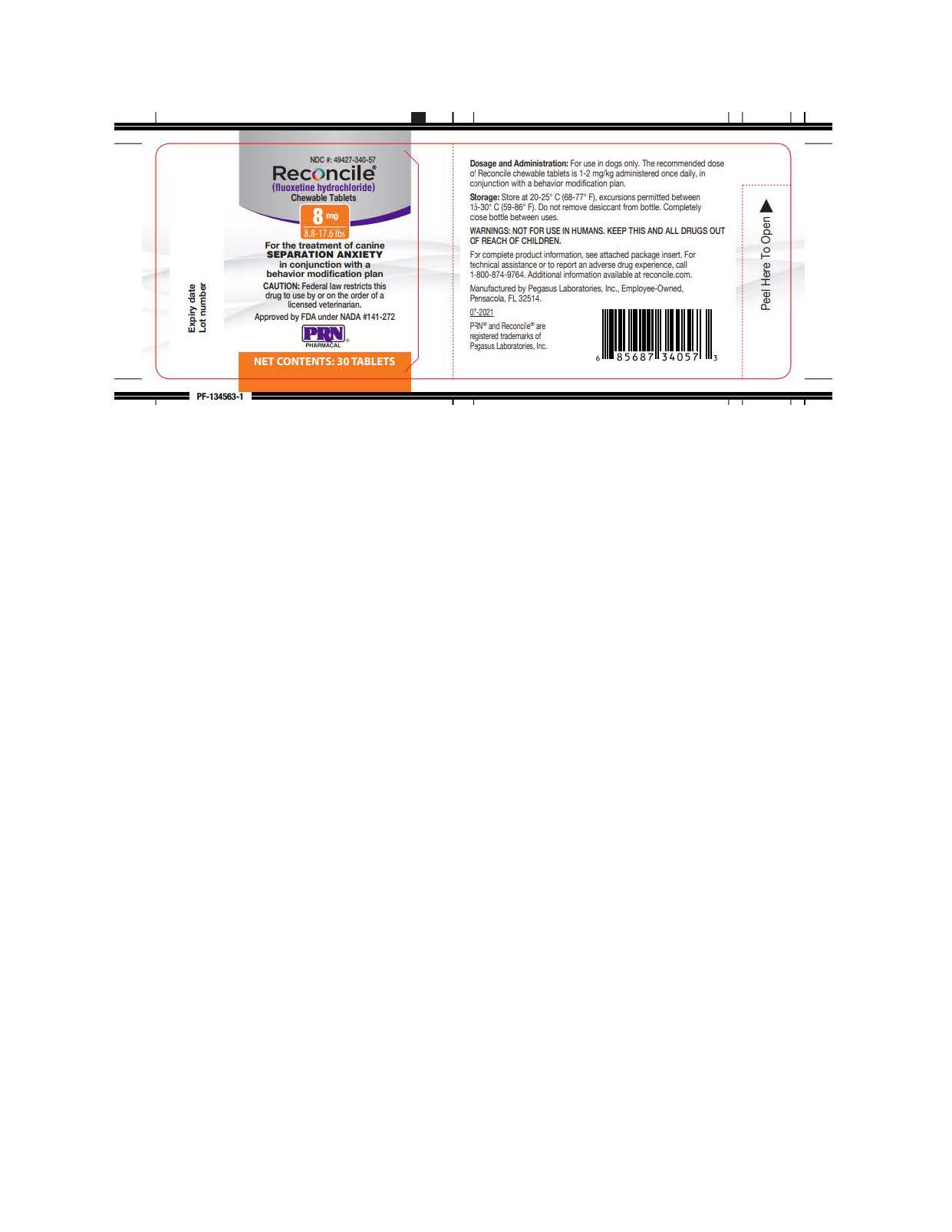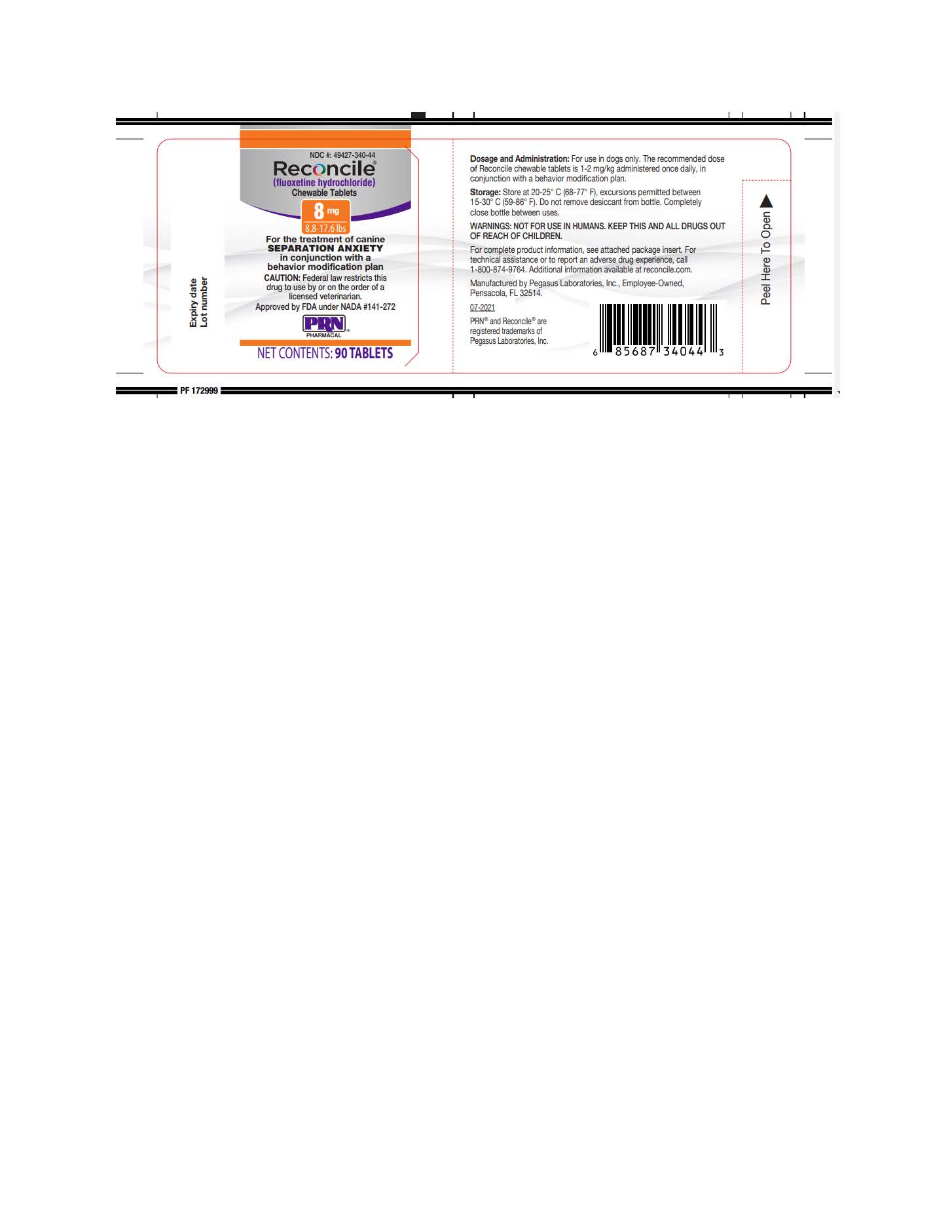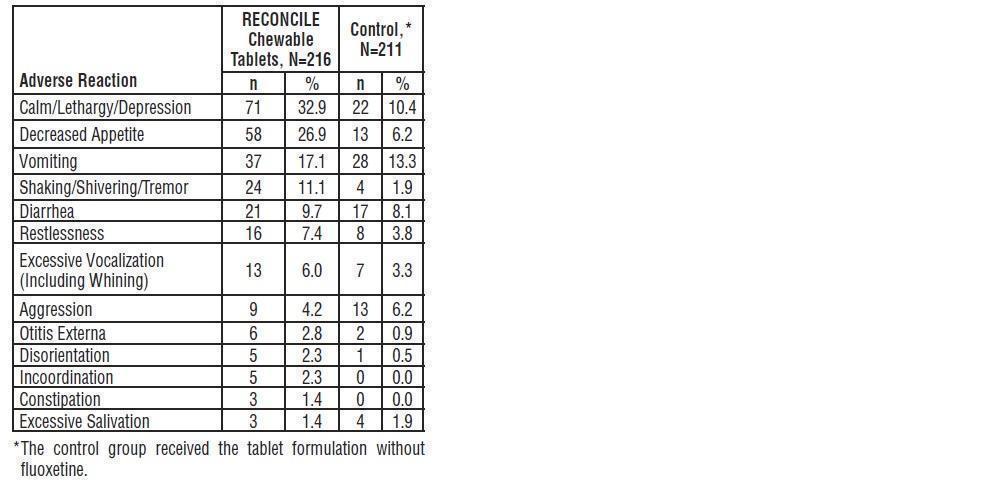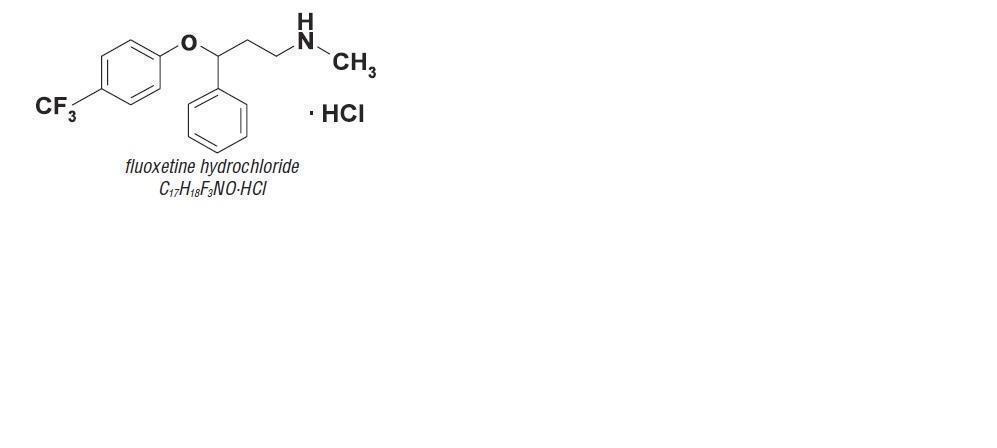 DRUG LABEL: RECONCILE
NDC: 49427-340 | Form: TABLET, CHEWABLE
Manufacturer: Pegasus Laboratories, Inc.
Category: animal | Type: PRESCRIPTION ANIMAL DRUG LABEL
Date: 20221229

ACTIVE INGREDIENTS: FLUOXETINE HYDROCHLORIDE 8 mg/1 1

Principal Display Panel

NDC: #49427-340-57; NDC: #49427-340-44
Reconcile®
(fluoxetine hydrochloride)
Chewable Tablets

8 mg
8.8 - 17.6 lbs

Approved by FDA under NADA #141-272

PRN Pharmacal

Net Contents: 30 or 90 Tablets

Indication:

For the treatment of canine SEPARATION ANXIETY in conjunction with a behavior modification plan

Dosage and Administration:

For use in dogs only. The recommended dose of Reconcile chewable tablets is 1-2 mg/kg administered once daily, in conjunction with a behavior modification plan.

Storage:

Store at 20-25° C (68-77° F), excursions permitted between 15-30° C (59-86° F). Do not remove desiccant from bottle. Completely close bottle between uses.

WARNINGS:

NOT FOR USE IN HUMANS. KEEP THIS AND ALL DRUGS OUT OF REACH OF CHILDREN.

Additional Information:

For complete product information, see attached package insert. For technical assistance or to report an adverse drug experience, call 1-800-874-9764. Additional information available at reconcile.com.

Manufactured by Pegasus Laboratories, Inc., Employee-Owned, Pensacola, FL 32514.

07-2021

PRN® and Reconcile® are registered trademarks of Pegasus Laboratories, Inc.

CLIENT INFORMATION

Your veterinarian has chosen to prescribe RECONCILE chewable tablets along with a simple training plan (a behavioral modification plan) to treat the separation anxiety that affects your dog. Please read this leaflet, which describes the use of RECONCILE chewable tablets. If you have any questions about this information, please consult your veterinarian. Additional information can be found at www.reconcile.com.

What are RECONCILE chewable tablets?

RECONCILE is a chewable, flavored tablet that you give to your dog once a day to treat separation anxiety. It is administered in conjunction with a simple training plan. RECONCILE chewable tablets are for use in dogs and puppies 6 months of age or older, and 8.8 pounds (4.0 kilograms) or greater.

What is Separation Anxiety?

Separation anxiety is a disease in which affected dogs may exhibit certain problematic behaviors when left alone. Dogs are social animals, and naturally become bonded to family members in their household. When separated from these people, certain dogs may experience distress and engage in unacceptable behaviors as a result of the anxiety of separation. The more common behaviors associated with separation anxiety include destruction of household items, barking and/or whining, soiling or urinating in the house, heavy drooling and attempting to escape. RECONCILE chewable tablets, when administered in conjunction with a simple training plan that you undertake at home, have been shown to reduce these detrimental behaviors exhibited by your dog.

What is a Simple Training Plan (Behavior Modification Plan), and why does my dog need one?

Your veterinarian will instruct you on how to incorporate simple training techniques, referred to as “behavior modification.” The combined use of these techniques with RECONCILE chewable tablets has been proven to work faster and better than training alone for the management of separation anxiety.

The simple training plan generally consists of several activities, such as:

- Adapting your dog to your coming and going behavior.
- Eaching your dog to sit and stay and, over time, to be content in your absence.
- Resisting the rewarding of inappropriate attention-seeking behaviors.
- Leaving your dog for short periods, and gradually increasing the time that the dog is left alone.

What does my veterinarian need to know about my dog before I give RECONCILE chewable tablets?

Your veterinarian is your dog’s healthcare expert and can make the best recommendation for medications for your dog. Key points of your visit may include the following:

- A thorough physical examination that may include laboratory analysis of blood and/or urine.
- A discussion of your dog's complete health history, training history and household environment.
- A discussion of any medications that you are giving now, or have given over the last several months to your dog, including over-the-counter and herbal supplements.

How should I give RECONCILE chewable tablets to my dog?

RECONCILE is a chewable flavored tablet that is readily consumed by most dogs. If your dog does not readily accept the RECONCILE chewable tablet, it may be offered in food or administered like other tablet medications. Follow your veterinarian’s directions regarding how much medication to administer.

If a dose is missed, the next scheduled dose should be given as prescribed. Do not increase or double the dose.

If more than the prescribed amount of RECONCILE chewable tablets are given, contact your veterinarian, who is the healthcare expert for your dog.

What can I expect from this therapy?

Some dogs may show improvement within 1-2 weeks of starting treatment with RECONCILE chewable tablets. Others may take as long as 8 weeks to show improvement. Your veterinarian will monitor the response to RECONCILE chewable tablets and the training plan. If no improvement is noted within 8 weeks, your veterinarian will discuss additional treatment plans for your dog.

RECONCILE chewable tablets work by making your dog more receptive to your training program. Although some dogs may appear calmer while on RECONCILE chewable tablets, it does not act as a sedative.

What side effects might occur while my dog is taking RECONCILE chewable tablets?

As with all medications, side effects may occur. Your veterinarian can best describe these for you and discuss what to do if you observe any unexpected effects or unusual behavior in your dog. The most serious side effect is seizures (convulsions), which in rare and severe cases can result in death. Based on clinical field studies, some animals may appear more calm or lethargic. Additional side effects that may be observed include: decreased appetite, vomiting, shaking or shivering, diarrhea, restlessness, excessive vocalization or whining, aggression, ear infec-tions, disorientation, incoordination, constipation, excessive salivation and weight loss. Since the introduction of RECONCILE, additional side effects reported are anxiety, dilated pupils, panting and confusion.

Can other medications be given while my pet is taking RECONCILE chewable tablets?

Yes, RECONCILE chewable tablets have been given safely with a wide variety of routinely administered products and medications, including vaccines, antibiotics, anti-inflammatories and products used for the control of fleas, intestinal worms and heartworms. There are a few products and medications that you should not give to your dog before, during or after treatment with RECONCILE chewable tablets because together, they can cause serious side effects. Your veterinarian should be made aware of all products, including over-the-counter and herbal supplements, that you intend to administer to your dog.

What else should I know about RECONCILE chewable tablets?

RECONCILE chewable tablets are not for use in humans. As with all medications, keep RECONCILE chewable tablets out of reach of children.

How Supplied:

RECONCILE is supplied in 8mg, 16mg, 32mg and 64mg strengths; as 30 or 90 tablets per bottle, with a child-resistant cap.

Approved by FDA under NADA #141-272.

Close the lid tightly between uses and keep the desiccant in the bottle until the medication is finished.

Store at 68-77°F (20-25°C). Temporary periods of time outside of this range between 59-86°F (15-30°C) are permitted.

If you have questions regarding the use of this product, consult your veterinarian, your pet’s healthcare expert. For technical assistance or to report an adverse drug experience, call 1-800-874-9764. Additional information can be found at www.reconcile.com.

Caution:

Federal law restricts this drug to use by or on the order of a licensed veterinarian.

Description:

RECONCILE is a chewable, flavored tablet that contains fluox-etine hydrochloride. RECONCILE chewable tablets are available in 8, 16, 32, and 64 mg tablet strengths for oral administration to dogs. The active ingredient in RECONCILE chewable tablets is fluoxetine hydrochloride, a selective serotonin reuptake inhibitor (SSRI). The molecular weight of fluoxetine is 345.79. The structural formula is depicted below.

Indications:

RECONCILE chewable tablets are indicated for the treatment of canine separation anxiety in conjunction with a behavior modification plan.

Dosage and Administration:

The recommended dose of RECONCILE chewable tablets is 1-2 mg/kg (0.5-0.9 mg/lb) administered once daily, in conjunction with a behavior modification plan. A typical behavior modification plan consists of the pet owner implementing standard training techniques based on principles such as rewarding appropriate behavior; coming and going in a manner that does not elicit inappropriate responses from the dog; and teaching the dog to be content while alone.

Table 1: Recommended Dose of RECONCILE Chewable Tablets

Dog Weight | Dog Weight | No. of Tablets/Day | Tablet Strength (mg)
(lb) | (kg)
8.8 - 17.6 | 4.0 - 8.0 | 1 | 8
17.7 - 35.2 | 8.1 - 16.0 | 1 | 16
35.3 - 70.4 | 16.1 - 32.0 | 1 | 32
70.5 - 140.8 | 32.1 - 64.0 | 1 | 64

The effectiveness and safety of RECONCILE chewable tablets was demonstrated in a field study in client-owned dogs (see EFFECTIVENESS and ADVERSE REACTIONS). At the end of the 8-week study, 73% of dogs treated with RECONCILE chewable tablets showed significant improvement (p=0.010), as compared to behavior modification alone (51%). During the course of therapy, 42% of dogs showed improvement within the first week, which was significantly greater (p=0.005) than with behavior modification alone (18%). The patient’s response to therapy should be monitored. If no improvement is noted within 8 weeks, case management should be reevaluated.

The effectiveness and clinical safety of RECONCILE chewable tablets for long-term use (i.e. for more than 8 weeks) has not been evaluated. RECONCILE chewable tablets were evaluated at the recommended label dose for one year in a laboratory safety study in dogs (see ANIMAL SAFETY).

Professional judgment should be used in monitoring the patient’s response to therapy to determine the need to continue treatment with RECONCILE chewable tablets beyond 8 weeks. To discontinue therapy, it is not necessary to taper or reduce doses because of the long half-life of this product. Continued behavioral modification is recommended to prevent recurrence of the clinical signs.

RECONCILE chewable tablets are readily consumed by dogs or can be administered like other tablet medications, and can be given with or without food.

Professional discretion should be used in determining the need for dose reduction in the event of a possible adverse reaction. Approximately half of patients tolerate a return to the previous dose after 1-2 weeks on a reduced schedule (see ADVERSE REACTIONS).

If a dose is missed, the next scheduled dose should be adminis-tered as prescribed. Do not increase or double the dose.

Contraindications:

RECONCILE chewable tablets are contraindicated for use in dogs with epilepsy or a history of seizures. RECONCILE chewable tablets should not be given concomitantly with drugs that lower the seizure threshold (e.g., phenothiazines such as acepromazine or chlorpromazine).

RECONCILE chewable tablets should not be given in combination with a monoamine oxidase inhibitor (MAOI) [e.g., selegiline hydrochloride (L-deprenyl) or amitraz], or within a minimum of 14 days of discontinuing therapy with an MAOI.

RECONCILE chewable tablets are contraindicated in dogs with a known hypersensitivity to fluoxetine HCl or other SSRIs.

Because fluoxetine and its major metabolite, norfluoxetine, have long half-lives, a 6-week washout interval should be observed following discontinuation of therapy with RECONCILE chew-able tablets prior to the administration of any drug that may adversely interact with fluoxetine or norfluoxetine.

Warnings:

Not for use in humans. Keep out of reach of children. In case of accidental ingestion seek medical attention immediately. In humans, the most common symptoms associated with over dosage include seizures, somnolence, nausea, tachycardia, and vomiting. In case of ingestion by a human, contact a physician immediately. For a copy of the Safety Data Sheet (SDS) or to report adverse reactions call 1-800-874-9764.

Precautions:

RECONCILE chewable tablets are not recommended for the treatment of aggression. RECONCILE chewable tablets have not been clinically tested for the treatment of other behavioral dis orders. Studies to determine the effects of RECONCILE chewable tablets in breeding, pregnant, or lactating dogs and in patients less than 6 months of age have not been conducted.

Seizures may occur in dogs treated with RECONCILE chewable tablets, even in dogs without a history of epilepsy or seizures (see ADVERSE REACTIONS).

Before prescribing RECONCILE chewable tablets, a comprehensive physical examination should be conducted to rule out causes of inappropriate behavior unrelated to separation anxiety. The examination should include a thorough history and assessment of the patient’s household environment and standard practice laboratory tests as appropriate for the patient’s age and health status. Veterinarians should be familiar with the risks and benefits of the treatment of behavioral disorders in dogs before initiating therapy. Inappropriate use of RECONCILE chewable tablets, i.e. in the absence of a diagnosis or without concurrent behavior modification, may expose the animal to un-necessary adverse reactions and may not provide any lasting benefit of therapy.

RECONCILE chewable tablets have not been evaluated with drugs that affect the cytochrome P450 enzyme system. RECONCILE chewable tablets should be used with caution when co-administered with any drug that affects the cytochrome P450 enzyme system (for example, ketaconazole). Studies to assess the interaction of RECONCILE chewable tablets with tricyclic antidepressants (TCAs) (for example, amitriptyline and clomipramine) have not been conducted. The minimum washout period to transition dogs from TCAs to RECONCILE chewable tablets has not been evaluated. Published pharmaco-kinetic data demonstrates that TCAs are cleared 4 days following discontinuation.^(1, 2)

Adverse Reactions:

In two North American multi-site field studies, which included a total of 427 dogs, the following adverse reactions were observed:

Seizures:

In one study, one of 112 dogs in the control group and three of 117 dogs that received RECONCILE chewable tablets experi-enced the serious adverse reaction of seizures. One of the three dogs treated with RECONCILE chewable tablets experienced two seizures 10 days after the end of therapy. Despite escalat-ing phenobarbital doses, the seizures continued and this dog died in status epilepticus approximately six months after the first seizure. Another of the three dogs treated with RECONCILE chewable tablets had experienced one seizure approximately 1½ years prior to study enrollment immediately after receiving head trauma. No additional seizures were reported to have oc-curred until 45 days after concluding treatment with RECONCILE chewable tablets. During the 1½-year period since the second seizure, this dogs seizure activity increased from single seizures to cluster seizures despite increasing doses of phenobarbital and the addition of oral potassium bromide and rectal diazepam. The third dog treated with RECONCILE chewable tablets and the control dog experienced one seizure 24 days and 35 days, respectively, after the start of therapy; no anticonvulsant therapy was initiated and no further seizures were reported in either dog.

In the second study, one of 99 dogs treated with RECONCILE chewable tablets and one of 99 dogs treated with the control tablet experienced the serious adverse reaction of seizures 9 and 27 days, respectively, after initiation of therapy. The dog treated with RECONCILE chewable tablets was subsequently diagnosed with vestibular disease and the control dog had a history of recurrent hind leg weakness.

In a European multi-site study, 234 dogs were treated with daily doses of fluoxetine chewable tablets ranging from 0.25 mg/kg to 4 mg/kg. One dog treated with a daily dose of 0.4 mg/kg for one month experienced one seizure one week after discontinuing therapy. No anticonvulsant therapy was initiated and no further seizures were reported.

Weight loss:

Of the dogs in the two North American field studies with body weight measurements throughout the study (n=196 and n=185 in the RECONCILE chewable tablets and control group, respectively), a 5% or greater weight loss (when compared to initial, pre-study body weight) was observed in 58 (29.6%) of dogs treated with RECONCILE chewable tablets and 24 (13.0%) of dogs in the control group. No dogs were withdrawn from clinical studies due to weight loss alone. The following table shows the number of dogs with weight loss, stratified by percent weight loss relative to initial body weight.

Table 2: Dogs with Weight Loss (stratified by percent loss relative to initial body weight)

Treatment Group | 5% to <10% Number (%) | 10% to <15% Number (%) | 15% Number (%)
RECONCILE chewable tablets | 44 (22.5%) | 13 (6.6%) | 1a (0.5%)
Control | 20 (10.8%) | 4 (2.2%) | 0 (0%)

aThis dog lost 20% of its initial body weight and was the same dog that died in status epilepticus.

Other adverse reactions:

Additional adverse reactions observed in dogs treated with RECONCILE chewable tablets at a rate of 1% or greater were:

Table 3: Adverse Reactions Reported in the North American Field Studies

Dose Reduction:

Twenty dogs in the RECONCILE chewable tablet group and five dogs in the control group required a reduction in dose due to unacceptable adverse reactions, generally anorexia, vomiting, shaking and depression. Lowering the dose eliminated or reduced the severity of these adverse reactions in the RECONCILE chewable tablet group only. Resumption of the full dose of RECONCILE chewable tablets resulted in a return of the initial adverse reactions in approximately half of the affected dogs. The majority of these adverse reactions were intermittent and mild. However, one dog experienced recurrence of severe adverse reactions, which necessitated withdrawal from the study for that
dog. Additionally, two dogs required a second dose reduction of RECONCILE chewable tablets. Effectiveness was maintained in a majority of those dogs in which a dose reduction was necessary.

Post Approval Experience (Rev. 2010):

The following adverse events are based on post-approval adverse drug experience reporting with RECONCILE chewable tablets. Not all adverse reactions are reported to FDA CVM. It is not always possible to reliably estimate the adverse event frequency or establish a causal relationship to product exposure using this data.

The following adverse events are listed in decreasing order of reported frequency: decreased appetite, depression/lethargy, shaking/shivering/tremor, vomiting, restlessness and anxiety, seizures, aggression, diarrhea, mydriasis, vocalization, weight loss, panting, confusion, incoordination, and hypersalivation.

For a copy of the Safety Data Sheet (SDS) or to report suspected adverse drug events, contact Pegasus Laboratories at 1-800- 874-9764. For additional information about adverse drug expe-rience reporting for animal drugs, contact FDA at 1-888-FDA-VETS or http://www.fda.gov/AnimalVeterinary/SafetyHealth.

Clinical Pharmacology:

Fluoxetine exerts its effect by inhibiting the reuptake of serotonin at the pre-synaptic neuron. Fluoxetine does not act as a sedative. Fluoxetine is well absorbed after oral administration (~72%). It is largely metabolized in the liver by cytochrome P-450 enzyme system to norfluoxetine, an equipotent SSRI that contributes to the efficacy of RECONCILE chewable tablets.

After a single dose, and also at steady state, calculations were made as follows:

Table 4: Single Dose* Pharmacokinetic Parameters of Fluoxetine Hydrochloride (mean ± standard error).

 | AUC0-∞ (µg•hr/mL) | cmax (ng/mL) | Tmax; (hr) | T1/2; (hr) | T1/2 Range (hr)
Fluoxetine | 1.388 (±0.137) | 126.6 (±12.3) | 1.8 (±0.2) | 6.2 (±0.8) | 3.0 - 12.9
Norfluoxetine | 11.44 (±0.74) | 138.3 (±9.6) | 12.8 (±1.7) | 49 (±3) | 33.0 - 64.0

*approximately 2 mg/kg body weight

In a 21-day study, fluoxetine was administered daily at a dose of 0.75, 1.5 and 3.0 mg/kg to laboratory Beagles. The maximum plasma concentration (Cmax) and area under the plasma concen-tration time curve (AUC) for fluoxetine were approximately dose proportional between 0.75 and 1.5 mg/kg, with a greater than dose proportional increase at 3 mg/kg. Norfluoxetine Cmax and AUC were generally dose proportional.

Although steady state appeared to be reached within 10 days in the 21-day study, a continuous increase in trough concentrations was observed in a one year, multiple-dose laboratory safety study. In this study, dogs administered a 1 mg/kg dose of fluoxetine had plasma fluoxetine concentrations that continued to increase over the one-year dosing period. A similar increase in concentrations was observed with norfluoxetine. This phenomenon was not observed at higher doses. During the one-year dosing interval and the subsequent two-month recovery period, there were no changes in the nature and fre-quency of adverse reactions observed as compared to those seen by Day 28 of fluoxetine administration.

Effectiveness:

In one randomized multi-centered, double-blinded, vehicle- controlled study of 8 weeks duration, 229 dogs were evaluated at 34 investigative sites in the United States and Canada. One hundred seventeen dogs were randomized to 1-2 mg/kg/day of RECONCILE chewable tablets and 112 dogs were randomized to the control group. Both groups underwent concurrent behavior modification. In seven of the eight weeks, the percent-age of dogs with improved overall separation anxiety scores was significantly higher (p ≤ 0.05) among dogs treated with RECONCILE chewable tablets compared to dogs that received the control tablet. At the end of the study, 73% of dogs treated with RECONCILE chewable tablets showed significant improvement (p=0.010) as compared to 51% of dogs treated with behavior modification alone.

Dogs treated with RECONCILE chewable tablets also showed improvement in destructive behavior, excessive vocalization, and restlessness over dogs that received the control tablet. In addition, dogs in both groups experienced improvement in inappropriate urination, inappropriate defecation, excessive salivation, excessive licking/grooming, shaking/shivering and depression. Overall separation anxiety severity scores improved more rapidly for dogs taking RECONCILE chewable tablets than those dogs receiving the control tablet. The same effect was also noted for the individual scores for excessive vocalization and depression.

Animal Safety:

In a one-year laboratory safety study, dogs were dosed daily at 1, 4.5, and 20 mg/kg/day of a gelatin capsule filled with fluoxetine powder. Based upon the results of a relative bioavailability study comparing the fluoxetine-filled capsule versus the RECONCILE chewable tablets, the corresponding equivalent doses were 0.87, 3.9 and 17.4 mg/kg/day of RECONCILE chewable tablets (where the average ratio of fluoxetine AUC values for RECONCILE chewable tablets/fluoxetine-filled capsule = 1.15).

Three of five female dogs in the 20 mg/kg group, died or were euthanatized during the first six months of the study. The high dose was decreased to 10 mg/kg/day (equivalent to 8.7 mg/kg/day of RECONCILE chewable tablets) for the last six months of the treatment, and all remaining dogs completed the study. One dog in the 1 mg/kg group (equivalent to 0.87 mg/kg/day of RECONCILE chewable tablets) and two dogs in the 20 mg/kg group (equivalent to 17.4 mg/kg/day of RECONCILE chewable tablets) experienced a seizure. Aggressive behavior, ataxia, salivation at dosing, hyperesthesia, nystagmus, thin body condition, weak-ness, lethargy, diarrhea and head tilt were also noted in the high dose group. Anorexia, tremors, decreased pupillary light response, mydriasis, vomiting, and decreased weight gain were observed in all treatment groups, but occurred more frequently in the high dose group. With the exception of decreased weight gain, all abnormal observations resolved by the end of a two-month recovery period. Evidence of phospholipidosis was noted in the lung, liver, adrenal glands, lymph nodes, spleen, retina and white blood cells of all groups, which resolved during the recovery period. Fluoxetine caused no marked or consistent effects on hematology, blood chemistries or urinalysis. Brady-cardia was absent on the electrocardiogram in the control and lowest dose groups, but was mildly present in a dose-dependent manner in the two higher dose groups. There were no effects noted on gross organ examination.

Storage Information:

Store at 20-25°C (68-77°F). Excursions permitted between 15- 30°C (59-86°F).

Do not remove desiccant from the bottle.

Completely close bottle between uses.

How Supplied:

RECONCILE is supplied in 8mg, 16mg, 32mg and 64mg strengths; as 30 or 90 tablets per bottle, with a child-resistant cap.

Approved by FDA under NADA #141-272

Manufactured by:

Pegasus Laboratories, Inc.

Employee-Owned

Pensacola, FL 32514

RECONCILE® is a registered trademark of Pegasus Laboratories, Inc.

References:

^1 Plumb DC. Amitriptyline. Veterinary Drug Handbook 5th Edition (Pocket Edition). Iowa State Press. Ames, IA. Page 39, 2002.
^2 Hewson CJ, et.al. The pharmacokinetics of clomipramine and desmethylclomipramine in dogs: parameter estimates following a single oral dose and 28 consecutive daily doses of clomipramine. J Vet Pharmacol Therap 21:214-222, 1998.